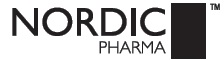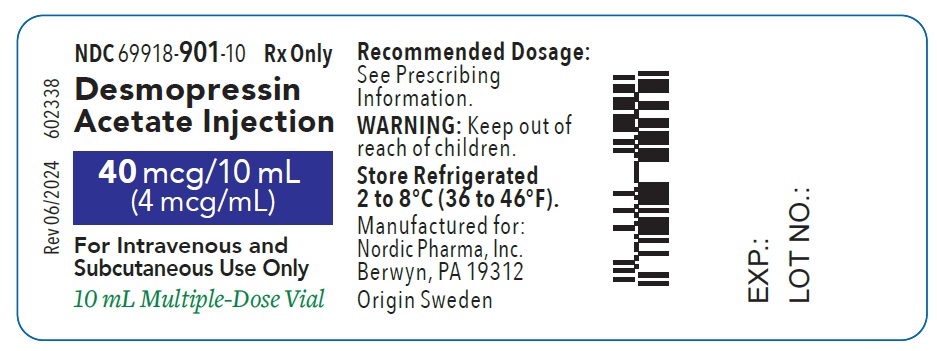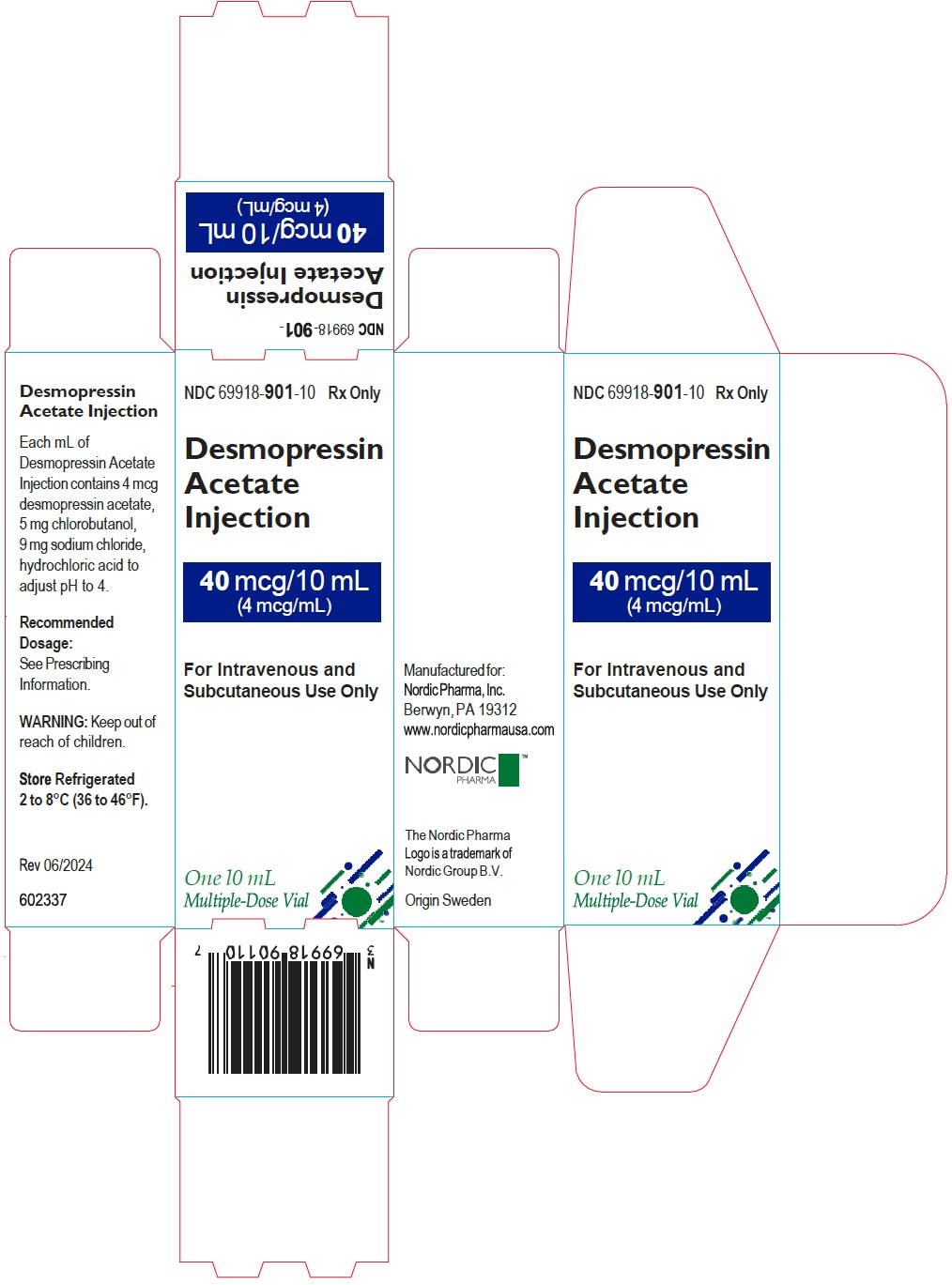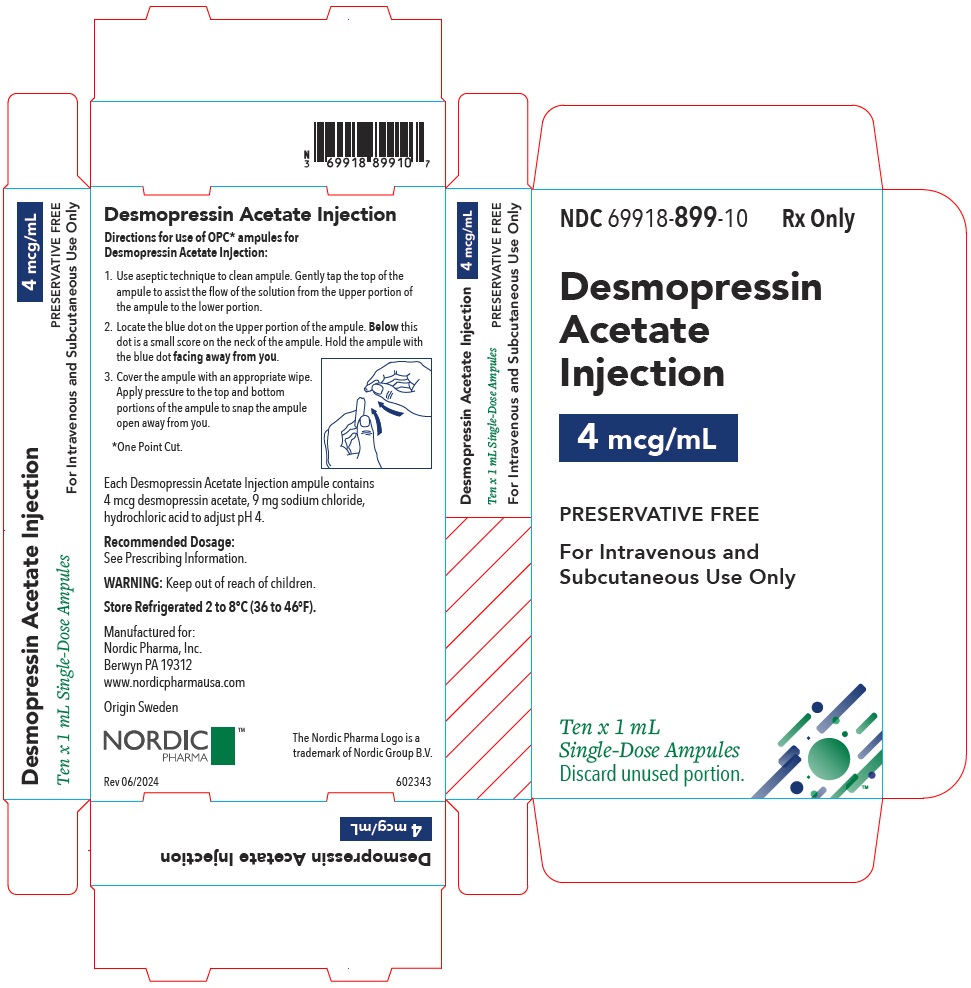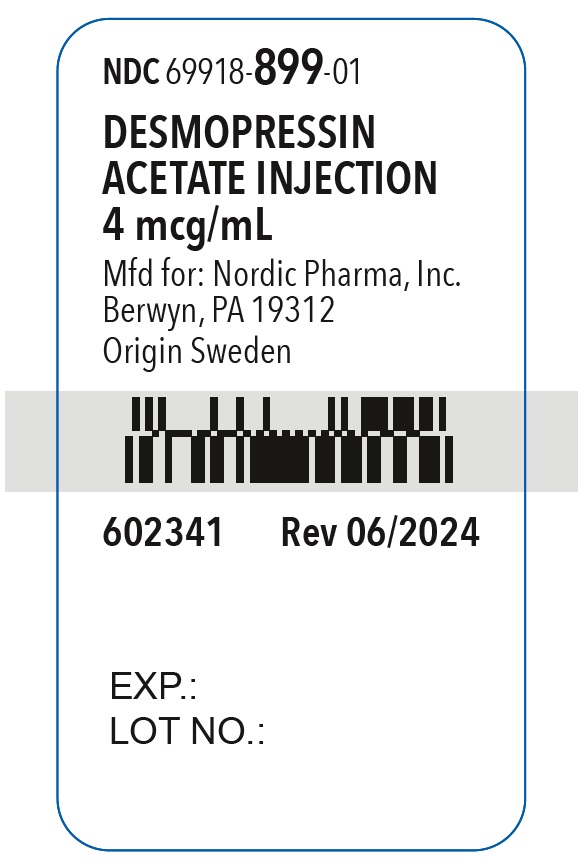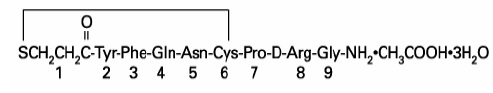 DRUG LABEL: Desmopressin Acetate
NDC: 69918-901 | Form: SOLUTION
Manufacturer: Nordic Pharma, Inc.
Category: prescription | Type: HUMAN PRESCRIPTION DRUG LABEL
Date: 20251024

ACTIVE INGREDIENTS: Desmopressin Acetate 4 ug/1 mL
INACTIVE INGREDIENTS: Sodium Chloride; Hydrochloric Acid; Chlorobutanol

HIGHLIGHTS OF PRESCRIBING INFORMATION

These highlights do not include all the information needed to use DESMOPRESSIN ACETATE INJECTION safely and effectively. See full prescribing information for DESMOPRESSIN ACETATE INJECTION.
DESMOPRESSIN ACETATE injection, for intravenous or subcutaneous use
Initial U.S. Approval: 1978

WARNING: HYPONATREMIA

See full prescribing information for complete boxed warning.

- Desmopressin acetate can cause hyponatremia, which may be life-threatening if severe. (5.1)
- Desmopressin acetate is contraindicated in patients at increased risk of severe hyponatremia, such as patients with excessive fluid intake, illnesses that can cause fluid or electrolyte imbalances, and in those using loop diuretics or systemic or inhaled glucocorticoids. (4, 5.1)
- Ensure serum sodium concentration is normal before starting or resuming desmopressin acetate. Measure serum sodium within 1 week and approximately 1 month after starting therapy and periodically during treatment. More frequently monitor serum sodium in patients 65 years of age and older and in patients at increased risk of hyponatremia. (2.1, 5.1)
- If hyponatremia occurs, interrupt or discontinue desmopressin acetate. (5.1)

1 INDICATIONS AND USAGE

Desmopressin acetate injection is a vasopressin analog used for:

- Central Diabetes Insipidus - as antidiuretic replacement therapy in the management of central (cranial) diabetes insipidus and for the management of the temporary polyuria and polydipsia following head trauma or surgery in the pituitary region. (1.1)
- Hemophilia A- for patients with factor VIII coagulant activity levels greater than 5% to maintain hemostasis during surgical procedures and postoperatively or reduce bleeding with episodes of spontaneous or traumatic injuries such as hemarthroses, intramuscular hematomas, or mucosal bleeding. (1.2)
- von Willebrand’s disease (Type I) - for patients with mild to moderate disease with factor VIII levels greater than 5% to maintain hemostasis during surgical procedures or traumatic injuries such as hemarthroses, intramuscular hematomas, or mucosal bleeding. (1.3)

Limitations of Use

- Desmopressin acetate is ineffective and not indicated for the treatment of nephrogenic diabetes insipidus. (1.3)
- von Willebrand’s disease (severe Type I) - not indicated for the treatment of patients with severe Type I von Willebrand’s disease and when there is evidence of an abnormal molecular form of factor VIII antigen. (1.3)

2 DOSAGE AND ADMINISTRATION

- Diabetes Insipidus: The daily dose is 2 mcg to 4 mcg administered as one or two divided doses by subcutaneous or intravenous injection. The dosage must be determined for each patient and adjusted according to the pattern of response. (2.1)
- Hemophilia A and von Willebrand’s Disease (Type I): 0.3 mcg/kg (to a maximum of 20 mcg) administered by intravenous infusion. Dilute dose as appropriate. (2.1)
- See Full Prescribing Information for instructions on reconstitution, preparation, and administration. (2)

3 DOSAGE FORMS AND STRENGTHS

Injection: 4 mcg/mL in 1 mL single-dose ampule and 40 mcg/10 mL (4 mcg/mL) in a multiple-dose vial. (3)

4 CONTRAINDICATIONS

- Known hypersensitivity to desmopressin acetate or to any of the components (4)
- Moderate to severe renal impairment defined as a creatinine clearance below 50 mL/min (4)
- Hyponatremia or a history of hyponatremia (4)
- Known or suspected syndrome of inappropriate antidiuretic hormone (SIADH) secretion (4)
- Polydipsia (4)
- Concomitant use with loop diuretics or systemic or inhaled glucocorticoids (4)
- During illnesses that can cause fluid or electrolyte imbalance (4)
- Heart failure or uncontrolled hypertension (4)

5 WARNINGS AND PRECAUTIONS

- Hypotension and Hypertension: May cause hypotension with compensatory increase in heart rate or hypertension. Monitor blood pressure during desmopressin acetate administration, especially in patients with heart disease. (5.2)
- Increased Risk of Thrombosis in Patients with von Willebrand’s Disease Type IIB: Use of desmopressin acetate in patients with Type IIB von Willebrand’s disease may cause thrombosis due to platelet aggregation. (5.3)
- Hypersensitivity Reactions: Severe reactions have occurred. Monitor for reactions during administration and interrupt if reaction occurs. (5.4)
- Fluid Retention: Fluid retention can worsen underlying conditions that are susceptible to volume status. Not recommended in patients at risk for increased intracranial pressure or with a history of urinary retention. (5.5)

6 ADVERSE REACTIONS

Common adverse reactions are abdominal cramps, burning pain, erythema, facial flushing, fluid retention, headache, hypersensitivity reactions, hypertension, hyponatremia, hyponatremic seizures, hypotension, nausea, swelling, tachycardia, and thrombotic events. (6)

To report SUSPECTED ADVERSE REACTIONS, contact Nordic Pharma, Inc. at 1-844-267-4641 or FDA at 1-800-FDA-1088 or www.fda.gov/medwatch.

7 DRUG INTERACTIONS

- Drugs that increase risk of hyponatremia: Require more frequent serum sodium monitoring. (7.1)
- Other vasoconstrictors: May require a reduction of the desmopressin acetate dosage. (7.2)

8 USE IN SPECIFIC POPULATIONS

- Pediatric Use: Initiate fluid intake restriction to prevent possible hyponatremia and water intoxication. (8.4)
- Geriatric Use: Carefully select dose and monitor renal function more frequently. (8.5)

FULL PRESCRIBING INFORMATION

WARNING: HYPONATREMIA

Desmopressin acetate can cause hyponatremia. Severe hyponatremia can be life-threatening, leading to seizures, coma, respiratory arrest, or death [see Warnings and Precautions (5.1)].

Desmopressin acetate is contraindicated in patients at increased risk of severe hyponatremia, such as patients with excessive fluid intake, illnesses that can cause fluid or electrolyte imbalances, and in those using loop diuretics or systemic or inhaled glucocorticoids [see Contraindications (4) and Warnings and Precautions (5.1)].

Ensure the serum sodium concentration is normal before starting or resuming desmopressin acetate. Measure serum sodium within 7 days and approximately 1 month after initiating therapy, and periodically during treatment. More frequently monitor serum sodium in patients 65 years of age and older and in patients at increased risk of hyponatremia [see Dosage and Administration (2.1) and Warnings and Precautions (5.1)].

If hyponatremia occurs, desmopressin acetate may need to be temporarily or permanently discontinued [see Warnings and Precautions (5.1)].

1 INDICATIONS AND USAGE

1.1 Central Diabetes Insipidus

Desmopressin acetate injection is indicated as antidiuretic replacement therapy in the management of central (cranial) diabetes insipidus and for the management of the temporary polyuria and polydipsia following head trauma or surgery in the pituitary region.

Limitations of Use:

Desmopressin acetate is ineffective and not indicated for the treatment of nephrogenic diabetes insipidus.

1.2 Hemophilia A

Desmopressin acetate injection is indicated for patients with hemophilia A with factor VIII coagulant activity levels greater than 5% without factor VIII antibodies to:

- Maintain hemostasis during surgical procedures and postoperatively
- Reduce bleeding with episodes of spontaneous or traumatic injuries such as hemarthroses, intramuscular hematomas, or mucosal bleeding.

1.3 von Willebrand’s Disease (Type I)

Desmopressin acetate injection is indicated for patients with mild to moderate von Willebrand’s disease (Type I) with factor VIII levels greater than 5% to:

- Maintain hemostasis during surgical procedures and postoperatively
- Reduce bleeding with episodes of spontaneous or traumatic injuries such as hemarthroses, intramuscular hematomas, or mucosal bleeding.

Limitations of Use

Desmopressin acetate is not indicated for the treatment of severe von Willebrand’s disease (Type I) and when there is evidence of an abnormal molecular form of factor VIII antigen [see Warnings and Precautions (5.2)].

2 DOSAGE AND ADMINISTRATION

2.1 Pretreatment Testing and On-Treatment Monitoring

Diabetes Insipidus

Prior to treatment with desmopressin acetate, assess serum sodium, urine volume and osmolality. Intermittently during treatment, assess serum sodium, urine volume and osmolality or plasma osmolality.

Hemophilia A

Prior to treatment with desmopressin acetate injection, verify that factor VIII coagulant activity levels are >5% and exclude the presence of factor VIII autoantibodies. Also assess serum sodium and aPTT prior to treatment. In certain clinical situations, it may be justified to try desmopressin acetate in patients with factor VIII levels between 2% to 5%; however, these patients should be carefully monitored.

von Willebrand’s Disease (Type I)

Prior to treatment with desmopressin acetate injection, verify that factor VIII coagulant activity levels are >5% and exclude severe von Willebrand’s disease (Type I) and presence of abnormal molecular form of factor VIII antigen. During treatment with desmopressin acetate injection, assess serum sodium, bleeding time, factor VIII coagulant activity, ristocetin cofactor activity, and von Willebrand antigen to ensure that adequate levels are being achieved.

For All Patients Receiving Repeated Doses: Restrict free water intake and monitor for hyponatremia.
Ensure that serum sodium is normal prior to initiating or resuming treatment with desmopressin acetate injection.

2.2 Recommended Dosage

Initiate fluid restriction during treatment with desmopressin acetate injection [see Warnings and Precautions (5.1), Use in Specific Populations (8.4, 8.5)].

Diabetes Insipidus:

Treatment naïve patients: The recommended starting daily dosage is 2 mcg to 4 mcg administered as one or two divided doses by subcutaneous or intravenous injection. Do not dilute desmopressin acetate injection for the Diabetes Insipidus population. The morning and evening doses should be separately adjusted for an adequate diurnal rhythm of water turnover. Adjust dose based upon response to treatment estimated by two parameters: adequate duration of sleep and adequate, not excessive, water turnover.

Patients changing from intranasal desmopressin: The recommended starting dose of desmopressin acetate injection is 1/10th the daily maintenance intranasal dose administered by subcutaneous or intravenous injection as one or two divided doses.

Hemophilia A and von Willebrand’s Disease (Type I):

The recommended dosage is 0.3 mcg/kg actual body weight (to a maximum of 20 mcg) administered by intravenous infusion over 15 minutes to 30 minutes. If used preoperatively, administer 30 minutes prior to the procedure. If used to reduce spontaneous or traumatic bleeding, doses may be repeated after 8 hours to 12 hours and once daily thereafter, if needed, based upon clinical condition and von Willebrand factor and factor VIII levels. The necessity for repeat administration of desmopressin acetate or use of any blood products for hemostasis should be determined by laboratory response as well as the clinical condition of the patient.

Tachyphylaxis (lessening of response) with repeated administration (i.e., given more frequently than every 48 hours) may occur. The initial response is reproducible if desmopressin acetate is administered every 2 to 3 days.

2.3 Preparation and Administration for Patients with Hemophilia A and von Willebrand’s Disease (Type I)

Prepare the solution for infusion using aseptic technique. Parenteral drug products should be inspected visually for particulate matter and discoloration prior to administration, whenever solution and container permit. Withdraw the necessary volume of desmopressin acetate injection from the vial and dilute by adding to the infusion bag of 0.9% Sodium Chloride Injection, USP per Table 1. Dilute desmopressin acetate injection in sterile 0.9% Sodium Chloride Injection, USP and infuse slowly over 15 minutes to 30 minutes.

The volume of diluent is weight-based. See Table 1 for volume of diluent to use.

Table 1: Volume of Diluent Required
Patient Weight | Volume of 0.9% Sodium Chloride Injection, USP for dilution
10 kg or less | 10 mL
More than 10 kg | 50 mL

Monitor blood pressure and pulse during infusion.

2.4 Switching Between Desmopressin Acetate Formulations

Desmopressin acetate is also available as nasal spray and tablet dosage forms.

When switching between formulations, the below text is meant as guidance for starting dose. However, dose should always be titrated individually according to the diuresis (antidiuretic response) and electrolyte status (serum sodium) of the patient.

When switching from desmopressin acetate nasal spray to desmopressin acetate injection, the starting dose is one-tenth times the desmopressin acetate nasal spray dose.

When switching from desmopressin acetate tablets to desmopressin acetate injection, titrate dose individually according to the diuresis (antidiuretic response) and electrolyte status (serum sodium) due to the large variability in both PK and PD. Monitor patients closely during the initial dose titration period.

3 DOSAGE FORMS AND STRENGTHS

Injection: Desmopressin acetate is a sterile, aqueous, colorless solution available as:

- 4 mcg/mL in single-dose ampule
- 40 mcg/10 mL (4 mcg/mL) in multiple-dose vial

4 CONTRAINDICATIONS

Desmopressin acetate injection is contraindicated in patients with known hypersensitivity to desmopressin acetate or to any of the components of desmopressin acetate injection [see Warnings and Precautions (5.4), Adverse Reactions (6), Description (11)].

Desmopressin acetate injection is contraindicated in patients with the following conditions due to an increased risk of hyponatremia:

- Moderate to severe renal impairment defined as a creatinine clearance below 50 mL/min [see Use in Specific Populations (8.5, 8.6) and Clinical Pharmacology (12.3)].
- Hyponatremia or a history of hyponatremia [see Warnings and Precautions (5.1), Drug Interactions (7.1)], Use in Specific Populations (8.4, 8.5)].
- Known or suspected syndrome of inappropriate antidiuretic hormone (SIADH) secretion [see Warnings and Precautions (5.1)].
- Polydipsia [see Warnings and Precautions (5.1)].
- Concomitant use with loop diuretics [see Boxed Warning].
- Concomitant use with systemic or inhaled glucocorticoids [see Boxed Warning].
- During illnesses that can cause fluid or electrolyte imbalance, such as gastroenteritis, salt-wasting nephropathies, or systemic infection [see Boxed Warning].

Desmopressin acetate injection is contraindicated in patients with the following conditions because fluid retention increases the risk of worsening the underlying condition:

- Heart failure
- Uncontrolled hypertension

5 WARNINGS AND PRECAUTIONS

5.1 Hyponatremia

Desmopressin acetate injection can cause hyponatremia. Severe hyponatremia can be life-threatening if it is not promptly diagnosed and treated, leading to seizures, coma, respiratory arrest, or death [see Boxed Warning].

Desmopressin acetate injection is contraindicated in patients with hyponatremia (or a history of hyponatremia), with excessive fluid intake (e.g., polydipsia), using loop diuretics or systemic or inhaled glucocorticoids, with known or suspected SIADH, and/or illnesses that can cause fluid or electrolyte imbalances [see Contraindications (4), Drug Interactions (7)]. Avoid concomitant treatments that also cause hyponatremia.

Prior to starting or resuming desmopressin acetate injection, ensure that the serum sodium concentration is normal. Limit fluid intake to a minimum from 1 hour before administration until 8 hours after administration. Use of desmopressin acetate injection without concomitant reduction of fluid intake may lead to fluid retention and hyponatremia.

Monitor the serum sodium concentration within 1 week and approximately 1 month of initiating desmopressin acetate injection, and periodically thereafter [see Dosage and Administration (2.1)]. Base the frequency of serum sodium monitoring on the patient’s risk of hyponatremia.

Patients with conditions associated with fluid and electrolyte imbalance (i.e., cystic fibrosis, heart failure, and renal disorders), geriatric and pediatric patients, patients receiving concomitant treatments that also cause hyponatremia (i.e., tricyclic antidepressants, selective serotonin reuptake inhibitors, nonsteroidal anti-inflammatory drugs, chlorpromazine, opiate analgesics, carbamazepine, lamotrigine, thiazide diuretics and chlorpropamide), and patients with habitual or psychogenic polydipsia who may drink excessive amounts of water, may be at increased risk of hyponatremia [see Contraindications (4)].

If hyponatremia occurs, desmopressin acetate injection may need to be temporarily or permanently discontinued and treatment for the hyponatremia instituted, depending on the clinical circumstances, including the duration and severity of the hyponatremia.

5.2 Hypotension and Hypertension

Desmopressin acetate may cause hypotension (with compensatory increase in heart rate) or hypertension. Monitor blood pressure during desmopressin acetate administration, particularly in patients with a history of coronary artery insufficiency and/or hypertensive cardiovascular disease [see Adverse Reactions (6), Drug Interactions (7.2)].

5.3 Increased Risk of Thrombosis in Patients with von Willebrand’s Disease Type IIB

Use of desmopressin acetate in patients with Type IIB von Willebrand’s disease may result in platelet aggregation, thrombocytopenia, and possibly thrombosis.

5.4 Hypersensitivity Reactions

Hypersensitivity reactions including anaphylaxis have been reported with intravenous and intranasal desmopressin acetate, including cases of fatal anaphylaxis with intravenous desmopressin acetate. Desmopressin acetate injection is contraindicated in patients with known hypersensitivity to desmopressin acetate or to any of the components of desmopressin acetate injection [see Contraindications (4)]. It is not known whether antibodies to desmopressin acetate injection are produced after repeated injections. Monitor patients for signs or symptoms of hypersensitivity reactions during administration, interrupt treatment should a reaction occur, and manage medically. Permanently discontinue for serious hypersensitivity reaction [see Adverse Reactions (6)].

5.5 Fluid Retention

Desmopressin acetate injection can cause fluid retention, which can worsen underlying conditions that are susceptible to volume status. Patients with heart failure or uncontrolled hypertension may be at increased risk. Desmopressin acetate injection is not recommended in patients at risk for increased intracranial pressure or those with a history of urinary retention. Advise patients to limit fluid intake [see Patient Counseling Information (17)].

6 ADVERSE REACTIONS

The following clinically significant adverse reactions are described elsewhere in the labeling:

- Hyponatremia [see Contraindications, Warnings and Precautions (5.1)]
- Hypotension and Hypertension [see Warnings and Precautions (5.2)]
- Increased risk of thrombosis in patients with von Willebrand’s Disease Type IIB [see Warnings and Precautions (5.3)]
- Hypersensitivity reactions [see Warnings and Precautions (5.4)]
- Fluid retention [see Warnings and Precautions (5.5)]

The following adverse reactions have been identified during post-approval use of desmopressin acetate injection. Because these reactions are reported voluntarily from a population of uncertain size, it is not always possible to reliably estimate their frequency or establish a causal relationship to drug exposure.

Cardiovascular: Hypertension, hypotension, tachycardia, thrombotic events, fluid retention
Digestive: Nausea, abdominal cramps
Immune: Hypersensitivity reactions
Integumentary: Erythema, swelling, burning pain, facial flushing
Laboratory: Hyponatremia
Nervous: Headache, hyponatremic seizures

7 DRUG INTERACTIONS

7.1 Other Drugs that may Increase Risk of Hyponatremia

The concomitant administration of desmopressin acetate injection with other drugs that may increase the risk of water intoxication with hyponatremia, (e.g., tricyclic antidepressants, selective serotonin re-uptake inhibitors, chlorpromazine, opiate analgesics, thiazide diuretics, NSAIDs, lamotrigine, sulfonylureas, particularly chlorpropamide, oxybutynin and carbamazepine), requires more frequent serum sodium monitoring. Monitor serum sodium more frequently in patients taking desmopressin acetate injection concomitantly with these drugs and when doses of these drugs are increased [see Contraindications (4), Warnings and Precautions (5.1), Drug Interactions (7.1), Use in Specific Populations (8.4, 8.5)].

7.2 Other Vasoconstrictors

Desmopressin acetate injection can elevate blood pressure. Use of desmopressin acetate injection with other vasoconstrictors may require a reduction of the desmopressin acetate injection dosage [see Warnings and Precautions (5.2), Adverse Reactions (6)].

8 USE IN SPECIFIC POPULATIONS

8.1 Pregnancy

Risk Summary

Prolonged experience with desmopressin acetate injection in pregnant women over several decades, based on the available published literature and case reports, have not identified a drug associated risk of major birth defects, miscarriage or other adverse maternal or fetal outcomes.

In addition, in vitro studies with human placenta demonstrate poor placental transfer of desmopressin. No adverse developmental outcomes were observed in animal reproductive and developmental studies following administration of desmopressin acetate during organogenesis to pregnant rats and rabbits, at doses 130- and 110- times, respectively, the recommended dose of 18 mcg for a 60 kg patient, based on body surface area (mg/m^2).

The estimated background risk of major birth defects and miscarriage for the indicated population are unknown. In the US general population, the estimated background risk of major birth defects and miscarriage in clinically recognized pregnancies is 2-4% and 15-20%, respectively.

Clinical Considerations

Disease Associated Maternal and Embryo-fetal Risk:

Pregnant women with Hemophilia A or von Willebrand’s disease may be at an increased risk for bleeding diatheses and hemorrhagic events at delivery. An affected newborn may also be at risk of bleeding diatheses.

Data

Animal Data

In a developmental toxicity study in rats, desmopressin acetate was administered intravenously at doses of 9.68, 48.4, or 241 mcg/kg/day during the period of organogenesis (gestations days 7 to 17). Laparohysterectomy for fetal examinations were conducted on gestation day 20 for twenty females in each group; the remaining 10 females were allowed to litter in order to determine any postnatal effects that might be attributable to pre-natal treatment. No effects were seen on maternal and fetal survival, growth and morphology or post-natal offspring survival, growth, development, behavior and reproductive performance up to 241 mcg/kg/day (130 times the 18 mcg dose received by a 60 kg patient based on body surface area).

In an embryo-fetal development study and a pre- and postnatal development study in rabbits, desmopressin acetate was administered subcutaneously at doses of 2, 20 or 200 mcg/kg/day (embryo-fetal development) and 0.1, 1 or 10 mcg/kg/day (pre- and postnatal development) during the period of organogenesis (gestation days 6 to 18). No effects on maternal and fetal survival or morphology were observed in both studies at doses of up to 200 mcg/kg/day (215x the 18 mcg dose received by a 60 kg patient based on body surface area) nor were there effects in the pre- and postnatal development study on parturition, postnatal survival, growth, development or behavior, up to the highest dose tested of 10 mcg/kg/day (11 times the 18 mcg dose received by a 60 kg patient, based on body surface area).

8.2 Lactation

Risk Summary

Breastfeeding is not expected to result in clinically relevant exposure of the infant to desmopressin following maternal administration. Desmopressin is poorly transferred into human breastmilk at negligible amounts (see Data). There is no information on the effects of desmopressin on the breastfed child or on milk production. The developmental and health benefits of breastfeeding should be considered along with the mother’s clinical need for desmopressin acetate injection and any potential adverse effects on the breastfed child from desmopressin acetate injection or from the underlying maternal condition.

Data

The breast milk of lactating women was collected over 8 hours following administration of 300 mcg desmopressin nasal spray. The expected area under the plasma concentration time curve (AUC) of desmopressin following 300 mcg nasal spray is 2.4-fold higher to that of 4 mcg desmopressin acetate injection. Based on the measured concentrations of desmopressin following intranasal administration, the amounts of desmopressin that may be transferred to a breastfed infant correspond to 0.0001-0.005% of the dose administered.

8.4 Pediatric Use

The safety and effectiveness of desmopressin acetate have been established in pediatric patients 3 months of age and older with hemophilia A and von Willebrand’s disease and pediatric patients aged 12 years and older with diabetes insipidus. The safety and effectiveness of desmopressin acetate have not been established in infants less than 3 months of age with hemophilia A or von Willebrand’s disease or pediatric patients under 12 years of age with diabetes insipidus. Use in infants and pediatric patients will require careful fluid intake restriction to prevent possible hyponatremia and water intoxication. Fluid restriction should be discussed with the patient and/or guardian [see Warnings and Precautions (5.1)].

8.5 Geriatric Use

Clinical studies of desmopressin acetate injection did not include sufficient numbers of subjects aged 65 and over to determine whether they respond differently from younger subjects. Other reported clinical experience has not identified differences in responses between the elderly and younger patients. In general, dose selection should be cautious, usually starting at the low end of the dosing range, reflecting the greater frequency of decreased hepatic, renal, or cardiac function, and of concomitant disease or other drug therapy.

This drug is known to be substantially excreted by the kidney, and the risk of adverse reactions to this drug may be greater in patients with impaired renal function. Because elderly patients are more likely to have decreased renal function, care should be taken in dose selection, and it may be useful to monitor renal function. Desmopressin acetate is contraindicated in patients with moderate to severe renal impairment (defined as a creatinine clearance below 50 mL/min) [see Contraindications (4), Use in Specific Populations (8.6), Clinical Pharmacology (12.3)].

Use of desmopressin acetate injection in geriatric patients will require careful fluid intake restrictions to prevent possible hyponatremia and water intoxication. Fluid restriction should be discussed with the patient [see Warnings and Precautions (5.1)].

8.6 Renal Impairment

Desmopressin acetate is substantially excreted by the kidney, and the risk of adverse reactions may be greater in patients with renal impairment than patients with normal renal function. Desmopressin acetate is contraindicated in patients with estimated CLcr by Cockcroft-Gault equation less than 50 mL/min [see Contraindications (4), Clinical Pharmacology (12.3)].

10 OVERDOSAGE

Overdosage of desmopressin acetate injection leads to prolonged duration of action with an increased risk of water retention and hyponatremia. Signs of overdose may include headaches, abdominal cramps, nausea, facial flushing, confusion, drowsiness, problems with passing urine and rapid weight gain due to fluid retention [see Warnings and Precautions (5.1)]. In case of overdosage, the dosage should be reduced, frequency of administration decreased, or the drug withdrawn according to the severity of the condition, serum sodium assessed, and hyponatremia treated appropriately.

There is no known specific antidote for desmopressin acetate or desmopressin acetate injection 4 mcg/mL.

11 DESCRIPTION

Desmopressin acetate injection is a synthetic vasopressin analog for intravenous or subcutaneous use. It is chemically defined as follows:

Mol. Wt. 1183.34

Empirical Formula: C46H64N14O12S2•C2H4O2•3H2O

1-(3-mercaptopropionic acid)-8-D-arginine vasopressin monoacetate (salt) trihydrate.

Desmopressin acetate solution for injection is a sterile solution in a 1 mL single-dose ampule: Each mL contains 4 mcg of desmopressin acetate which is equivalent to 3.6 mcg of desmopressin free base. The inactive ingredients are sodium chloride, hydrochloric acid and water for injection. Sodium chloride is used to adjust tonicity. Hydrochloric acid is used to adjust pH.

Desmopressin acetate solution for injection is a sterile solution in a 10 mL multiple-dose vial: Each mL contains 4 mcg of desmopressin acetate which is equivalent to 3.6 mcg of desmopressin free base. The inactive ingredients are sodium chloride, chlorobutanol (5 mg per mL), hydrochloric acid and water for injection. Sodium chloride is used to adjust tonicity. Hydrochloric acid is used to adjust pH.

12 CLINICAL PHARMACOLOGY

12.1 Mechanism of Action

Desmopressin acetate increases plasma levels of factor VIII activity in patients with hemophilia and von Willebrand’s disease Type I.

The antidiuretic effects of desmopressin acetate are mediated by stimulation of vasopressin 2 (V2) receptors, thereby increasing water re-absorption in the kidney, and hence reducing urine production. Desmopressin acetate is a replacement hormone for antidiuretic hormone in the treatment of central diabetes insipidus. The change in structure of arginine vasopressin to desmopressin acetate resulted in increased duration of action and a decreased vasopressor action and decreased actions on visceral smooth muscle relative to the enhanced antidiuretic activity, so that clinically effective antidiuretic doses were usually below threshold levels for effects on vascular or visceral smooth muscle.

12.2 Pharmacodynamics

The response to desmopressin acetate of factor VIII activity and plasminogen activator is dose-related, with maximal plasma levels of 300 to 400 percent change from baseline obtained after infusion of 0.4 mcg/kg. The increase of factor VIII is rapid and evident within 30 minutes, reaching a maximum at a point ranging from 90 minutes to two hours. The duration of the hemostatic effect depends on the half-life for VIII:C which is about 8-12 hours. The percentage increase of factor VIII levels in patients with mild hemophilia A and von Willebrand’s disease was not significantly different from that observed in normal healthy individuals when treated with 0.3 mcg/kg of desmopressin acetate infused over 10 minutes.

The use of desmopressin acetate injection in patients with central diabetes insipidus reduces urinary output, increases urine osmolality, and decreases plasma osmolality.

12.3 Pharmacokinetics

Elimination

The geometric mean terminal half-life is 2.8 hours.

Metabolism

Desmopressin is not metabolized by human CYP450 system.

Excretion

After intravenous administration of 2 mcg, 52% of the dose was recovered in the urine within 24 hours as unchanged desmopressin.

Drug Interaction Studies

In vitro studies in human liver microsome preparations have shown that desmopressin does not inhibit the human CYP450 system. No in vivo interaction studies have been performed with desmopressin acetate injection.

Specific Populations

Patients with Renal Impairment

A pharmacokinetic study was conducted in subjects with normal renal function and patients with mild, moderate, and severe renal impairment (n=24, 6 subjects each group) with a single 2 mcg dose of desmopressin acetate intravenous injection. The geometric mean terminal half-life was 2.8 hours in subjects with normal renal function, and 4, 6.6, and 8.7 hours in patients with mild, moderate, and severe renal impairment, respectively. In patients with mild, moderate and severe renal impairment, mean desmopressin area under the plasma drug concentration time curve (AUC) was 1.5 fold, 2.4 fold and 3.6 fold higher, respectively compared to that of subjects with normal renal function.

13 NONCLINICAL TOXICOLOGY

13.1 Carcinogenesis, Mutagenesis, Impairment of Fertility

Studies with desmopressin have not been performed to evaluate carcinogenic potential. Desmopressin was not mutagenic in bacterial mutagenicity (Ames) and mouse lymphoma assays.

16 HOW SUPPLIED/STORAGE AND HANDLING

16.1 How Supplied

Desmopressin acetate injection is available as a sterile solution supplied as 4 mcg/ml in cartons of ten 1 ml single-dose, type 1 glass ampules (NDC 69918-899-10) and 40 mcg/10 ml (4 mcg/ml) in 10 ml multiple-dose vials, type 1 glass vial with rubber stopper and a flip off seal, (NDC 69918-901-10), each containing 4 mcg desmopressin acetate per ml.

16.2 Storage and Handling

Store refrigerated 2° to 8°C (36° to 46°F).

17 PATIENT COUNSELING INFORMATION

Hyponatremia and Fluid Restriction

- Inform patients that desmopressin acetate may cause severe hyponatremia, which may be life-threatening, if it is not promptly diagnosed and treated [see Warnings and Precautions (5.1)].
- Inform them about the signs and symptoms associated with hyponatremia, to undergo recommended serum sodium measurements, and to inform their health care provider about new medications.
- Advise patients to contact a healthcare provider if symptoms of hyponatremia occur.
- Discuss adjustment of fluid intake and monitoring of urine output with patients.

Manufactured for:
Nordic Pharma, Inc.
Berwyn, PA 19312

www.nordicpharmausa.com

The Nordic Pharma Logo is a trademark of Nordic Group B.V.
Origin Sweden
Rev 06/2024
602339

Package/Label Display Panel

NDC 69918-901-10

Rx Only

Desmopressin
Acetate Injection

40 mcg/10 mL
(4 mcg/mL)

For Intravenous and
Subcutaneous Use Only

10 mL Multiple-Dose Vial

NDC 69918-901-10

Rx Only

Desmopressin
Acetate
Injection

40 mcg/10 mL
(4 mcg/mL)

For Intravenous and
Subcutaneous Use Only

One 10 mL
Multiple-Dose Vial

NDC 69918-899-01

DESMOPRESSIN
ACETATE INJECTION

4 mcg/mL

NDC 69918-899-10

Rx Only

Desmopressin
Acetate
Injection

4 mcg/mL

PRESERVATIVE FREE

For Intravenous and
Subcutaneous Use Only

Ten x 1 mL
Single-Dose Ampules
Discard unused portion.